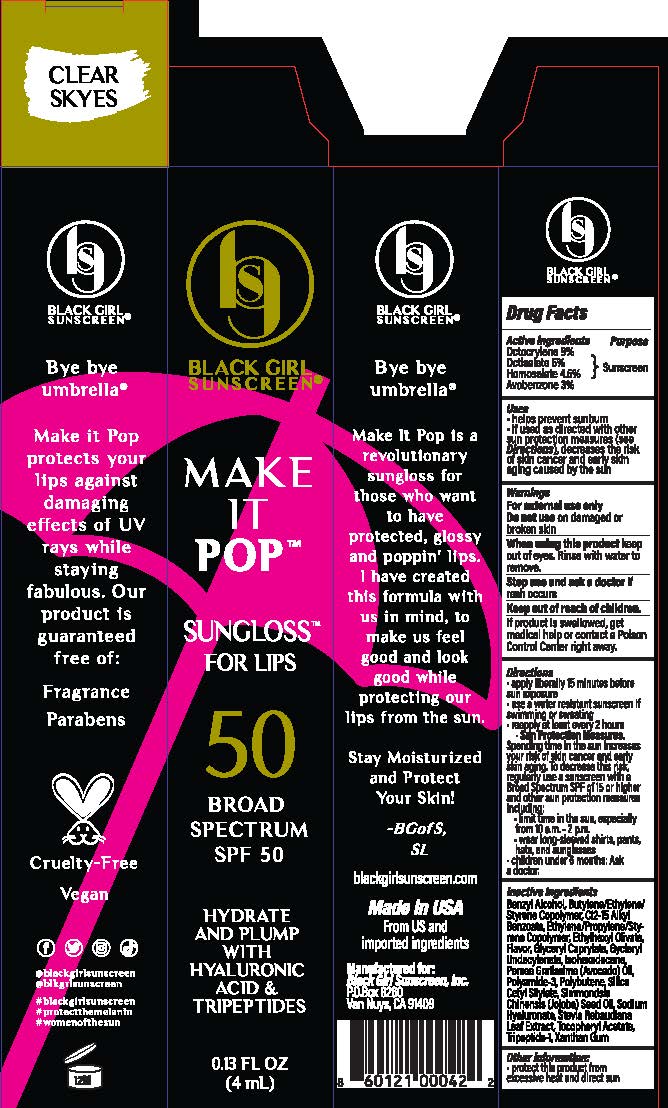 DRUG LABEL: Black Girl Sunscreen
NDC: 84204-0003 | Form: GEL
Manufacturer: Black Girl Sunscreen, LLC
Category: otc | Type: HUMAN OTC DRUG LABEL
Date: 20250115

ACTIVE INGREDIENTS: OCTISALATE 44.5 mg/1 mL; AVOBENZONE 26.7 mg/1 mL; HOMOSALATE 40.05 mg/1 mL; OCTOCRYLENE 80.1 mg/1 mL
INACTIVE INGREDIENTS: ALKYL (C12-15) BENZOATE; POLYAMIDE-3 (20000 MW); POLYBUTENE (1400 MW); STEVIA LEAF; 1-BUTENE; ETHYLENE; STYRENE; GLYCERYL CAPRYLATE; GLYCERYL 1-UNDECYLENATE; ISOHEXADECANE; AVOCADO OIL; HYALURONATE SODIUM; ALPHA-TOCOPHEROL ACETATE; XANTHAN GUM; PREZATIDE; PROPYLENE; JOJOBA OIL; BENZYL ALCOHOL

Black Girl Make it Pop SPF 50 Sun Gloss for Lips

Active ingredients

Octocrylene 9%

Octisalate 5%

Homosalate 4.5%

Avobenzone 3%

Purpose

Sunscreen

Uses

- helps prevent sunburn
- if used as directed with other sun protection measures (see Directions), decreases the risk of skin cancer and early skin aging caused by the sun

Warnings

For external use only

Do not use

on damaged or broken skin

When using this product

keep out of eyes. Rinse with water to remove

Stop use and ask a doctor

if rash occurs

Keep out of reach of children

If product is swalloed, get medical help or contact a Poison Control Center right away.

Directions

- apply liberally 15 minutes before sun exposure
- use a water resistant sunscreen if swimming or sweating
- reapply at least every 2 hours
- Sun Protection Measures: spending time in the sun increases your risk of skin cancer and early skin aging. To decrease this risk, regularly use a sunscreen with a Broad Spectrum SPF of 15 or higher and other sun protection measures including: • limit time in the sun, especially from 10 am to 2 pm • wear long-sleeved shirts, pants, hats, and sunglasses
- children under 6 months: ask a doctor

Inactive ingredients

Benzyl Alcohol, Butylene/Ethylene/Styrene Copolymer, C12-15 Alkyl Benzoate, Ethylene/Propylene/Styrene Copolymer, Ethylhexyl Olivate, Flavor, Glyceryl Caprylate, Glyceryl Undecylenate, Isohexadecane, Persea Gratissima (Avocado) Oil, Polyamide-3, Polybutene, Silica Cetyl Silylate, Simmondsia Chinensis (Jojoba) Seed Oil, Sodium Hyaluronate, Stevia Rebaudiana Leaf Extract, Tocopheryl Acetate, Tripeptide-1, Xanthan Gum

Other Information

protect this product from excessive heat and direct sun